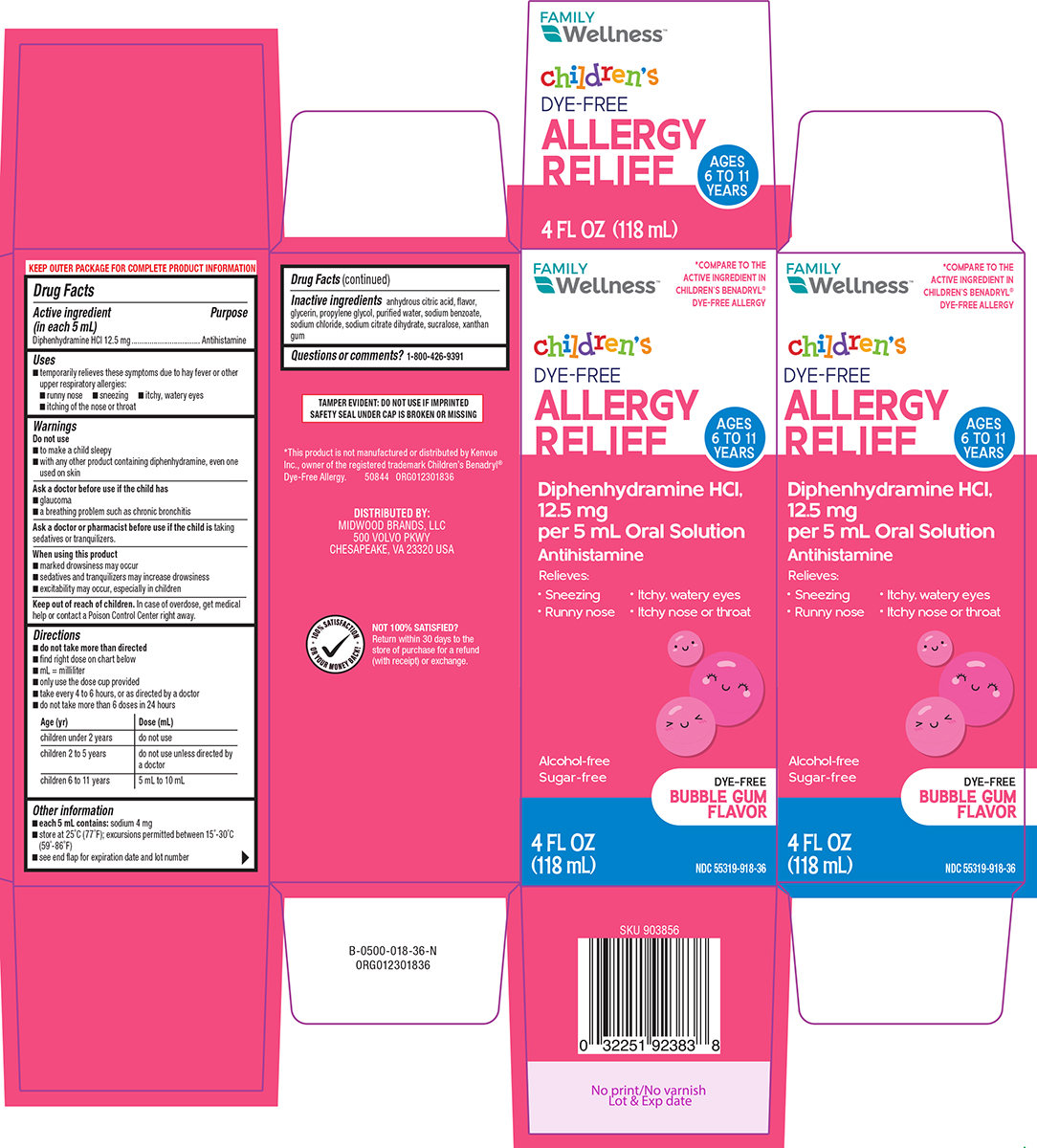 DRUG LABEL: Allergy Relief
NDC: 55319-918 | Form: SOLUTION
Manufacturer: Family Dollar Services Inc
Category: otc | Type: HUMAN OTC DRUG LABEL
Date: 20251210

ACTIVE INGREDIENTS: DIPHENHYDRAMINE HYDROCHLORIDE 12.5 mg/5 mL
INACTIVE INGREDIENTS: ANHYDROUS CITRIC ACID; GLYCERIN; PROPYLENE GLYCOL; WATER; SODIUM BENZOATE; SODIUM CHLORIDE; TRISODIUM CITRATE DIHYDRATE; SUCRALOSE; XANTHAN GUM

Family Wellness 44-018

Active ingredient (in each 5 mL)

Diphenhydramine HCl 12.5 mg

Purpose

Antihistamine

Uses

- temporarily relieves these symptoms due to hay fever or other upper respiratory allergies:
  - runny nose
  - sneezing
  - itchy, watery eyes
  - itching of the nose or throat

Warnings

Do not use

- to make a child sleepy
- with any other product containing diphenhydramine, even one used on skin

Ask a doctor before use if the child has

- glaucoma
- a breathing problem such as chronic bronchitis

Ask a doctor or pharmacist before use if the child is

taking sedatives or tranquilizers.

When using this product

- marked drowsiness may occur
- sedatives and tranquilizers may increase drowsiness
- excitability may occur, especially in children

Keep out of reach of children.

In case of overdose, get medical help or contact a Poison Control Center right away.

Directions

- do not take more than directed
- find right dose on chart below
- mL = milliliter
- only use the dose cup provided
- take every 4 to 6 hours, or as directed by a doctor
- do not take more than 6 doses in 24 hours

Age (yr) | Dose (mL)
children under 2 years | do not use
children 2 to 5 years | do not use unless directed by a doctor
children 6 to 11 years | 5 mL to 10 mL

Other information

- each 5 mL contains: sodium 4 mg
- store at 25ºC (77ºF); excursions permitted between 15º-30ºC (59º-86ºF)
- see end flap for expiration date and lot number

Inactive ingredients

anhydrous citric acid, flavor, glycerin, propylene glycol, purified water, sodium benzoate, sodium chloride, sodium citrate dihydrate, sucralose, xanthan gum

Questions or comments?

1-800-426-9391

Principal Display Panel

FAMILY
Wellness™

*COMPARE TO THE
ACTIVE INGREDIENT IN
CHILDREN'S BENADRYL®
DYE-FREE ALLERGY

children's
DYE-FREE
ALLERGY RELIEF

AGES
6 TO 11
YEARS

Diphenhydramine HCl,
12.5 mg
per 5 mL Oral Solution
Antihistamine

Relieves:

•Sneezing • Itchy, watery eyes
• Runny nose • Itchy nose or throat

Alcohol-free
Sugar-free

DYE-FREE
BUBBLE GUM
FLAVOR

4 FL OZ
(118 mL)

NDC 55319-918-36

TAMPER EVIDENT: DO NOT USE IF IMPRINTED
SAFETY SEAL UNDER CAP IS BROKEN OR MISSING

*This product is not manufactured or distributed by Kenvue
Inc., owner of the registered trademark Children’s Benadryl®
Dye-Free Allergy. 50844 ORG012301836

DISTRIBUTED BY:
MIDWOOD BRANDS, LLC
500 VOLVO PKWY
CHESAPEAKE, VA 23320 USA

NOT 100% SATISFIED?
Return within 30 days to the
store of purchase for a refund
(with receipt) or exchange.

Family Wellness 44-018